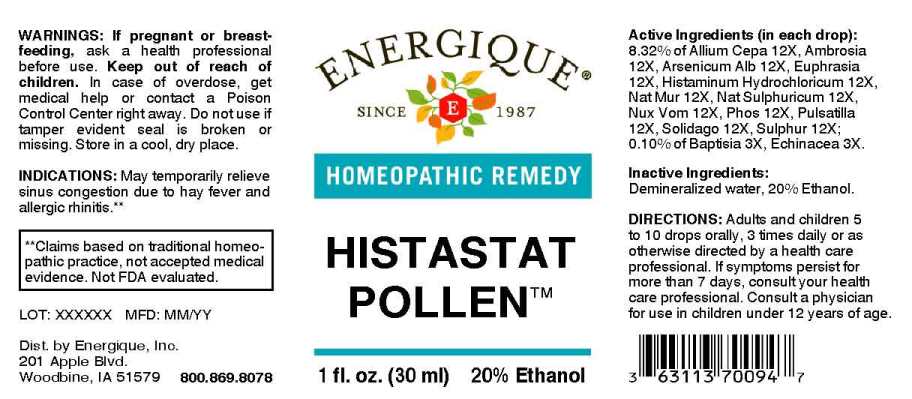 DRUG LABEL: Histastat Pollen
NDC: 44911-0674 | Form: LIQUID
Manufacturer: Energique, Inc.
Category: homeopathic | Type: HUMAN OTC DRUG LABEL
Date: 20230512

ACTIVE INGREDIENTS: BAPTISIA TINCTORIA ROOT 3 [hp_X]/1 mL; ECHINACEA ANGUSTIFOLIA WHOLE 3 [hp_X]/1 mL; EPINEPHRINE 12 [hp_X]/1 mL; ONION 12 [hp_X]/1 mL; AMBROSIA ARTEMISIIFOLIA WHOLE 12 [hp_X]/1 mL; ARSENIC TRIOXIDE 12 [hp_X]/1 mL; EUPHRASIA STRICTA 12 [hp_X]/1 mL; HISTAMINE DIHYDROCHLORIDE 12 [hp_X]/1 mL; SODIUM CHLORIDE 12 [hp_X]/1 mL; SODIUM SULFATE 12 [hp_X]/1 mL; STRYCHNOS NUX-VOMICA SEED 12 [hp_X]/1 mL; PHOSPHORUS 12 [hp_X]/1 mL; PULSATILLA PRATENSIS WHOLE 12 [hp_X]/1 mL; SCHOENOCAULON OFFICINALE SEED 12 [hp_X]/1 mL; BLACK MUSTARD SEED 12 [hp_X]/1 mL; SOLIDAGO VIRGAUREA FLOWERING TOP 12 [hp_X]/1 mL; SULFUR 12 [hp_X]/1 mL; WYETHIA HELENIOIDES ROOT 12 [hp_X]/1 mL
INACTIVE INGREDIENTS: WATER; ALCOHOL

DRUG FACTS:

ACTIVE INGREDIENTS:

(in each drop): 6.24% of Adrenalinum 12X, Allium Cepa 12X, Ambrosia Artemisiaefolia 12X, Arsenicum Album 12X, Euphrasia Officinalis 12X, Histaminum Hydrochloricum 12X, Natrum Muriaticum 12X, Natrum Sulphuricum 12X, Nux Vomica 12X, Phosphorus 12X, Pulsatilla 12X, Sabadilla 12X, Sinapis Nigra 12X, Solidago Virgaurea 12X, Sulphur 12X, Wyethia Helenioides 12X; 0.10% of Baptisia Tinctoria 3X, Echinacea 3X.

PURPOSE:

May temporarily relieve sinus congestion, runny nose, and sneezing.**

**Claims based on traditional homeopathic practice, not accepted medical evidence. Not FDA evaluated.

WARNINGS:

If pregnant or breast-feeding, ask a health professional before use.

Keep out of reach of children. In case of overdose, get medical help or contact a Poison Control Center right away.

Do not use if tamper evident seal is broken or missing.

Store in a cool, dry place.

KEEP OUT OF REACH OF CHILDREN:

In case of overdose, get medical help or contact a Poison Control Center right away.

DIRECTIONS:

Adults and children 5 to 10 drops orally, 3 times daily or as otherwise directed by a health care professional. If symptoms persist for more than 7 days, consult your health care professional. Consult a physician for use in children under 12 years of age.

INDICATIONS:

May temporarily relieve sinus congestion, runny nose, and sneezing.**

**Claims based on traditional homeopathic practice, not accepted medical evidence. Not FDA evaluated.

INACTIVE INGREDIENTS:

Demineralized water, 20% Ethanol.

QUESTIONS:

Dist. by Energique, Inc.

201 Apple Blvd.

Woodbine, IA 51579 800.869.8078

PACKAGE LABEL DISPLAY:

ENERGIQUE

SINCE 1987

HOMEOPATHIC REMEDY

HISTASTAT POLLEN

1 fl. oz. (30 ml)